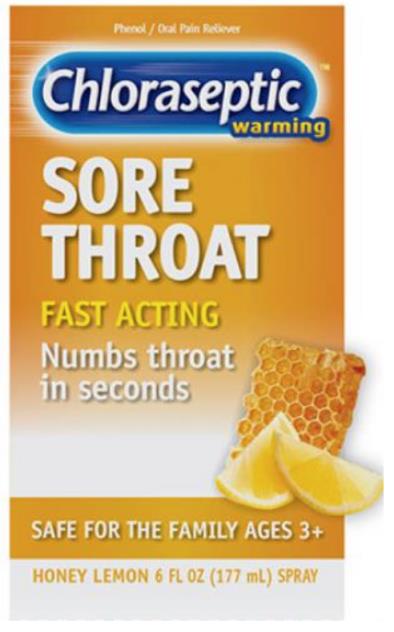 DRUG LABEL: Chloraseptic Warming Sore Throat
NDC: 67172-212 | Form: SPRAY
Manufacturer: Prestige Brands Holdings, Inc.
Category: otc | Type: HUMAN OTC DRUG LABEL
Date: 20241025

ACTIVE INGREDIENTS: PHENOL 3.5 mg/0.7 mL
INACTIVE INGREDIENTS: ANHYDROUS CITRIC ACID; FD&C YELLOW NO. 5; FD&C YELLOW NO. 6; GLYCERIN; WATER; SACCHARIN SODIUM; SODIUM CITRATE; SUCRALOSE

Chloraseptic Warming Sore Throat Spray

Drug Facts

Active ingredient

Phenol 1.4%

Purpose

Oral pain reliever

Uses

for the temporary relief of occasional minor irritation, pain, sore mouth and sore throat.

Warnings

Sore Throat Warning: Severe or persistent sore throat or sore throat accompanied by high fever, headache, nausea, and vomiting may be serious. Consult a doctor promptly. Do not use more than 2 days or give to children under 3 years of age unless directed by a doctor.

When using this product

do not exceed recommended dosage.

Stop use and ask a doctor or dentist if

- sore mouth symptoms do not improve in 7 days
- irritation, pain or redness persists or worsens
- swelling, rash or fever develops

If pregnant or breast-feeding,

ask a health professional before use.

Keep out of reach of children.

If more than used for minor mouth or throat pain is accidentally swallowed, get medical help or contact a Poison Control Center (1-800-222-1222) right away.

Directions

Adults and children 3 years of age and older:

- Apply to the affected area (one spray)
- Allow to remain in place for at least 15 seconds, then spit out
- Use every 2 hours or as directed by a doctor or dentist
  Children under 12 years of age should be supervised in the use of this product
  Children under 3 years of age: consult a doctor or dentist

Other information

- store at room temperature
- check expiration date before using
- contains FD&C yellow 5 (tartrazine) as a color additive

Inactive ingredients

caramel color, citric acid, FD&C yellow no. 5, FD&C yellow no.6, glycerin, flavors, purified water, saccharin sodium, sodium citrate, sucralose

Questions?

1-800-552-7932

PRINCIPAL DISPLAY PANEL

Chloraseptic
warming
SORE THROAT
HONEY LEMON 6 FL OZ (177 mL) SPRAY